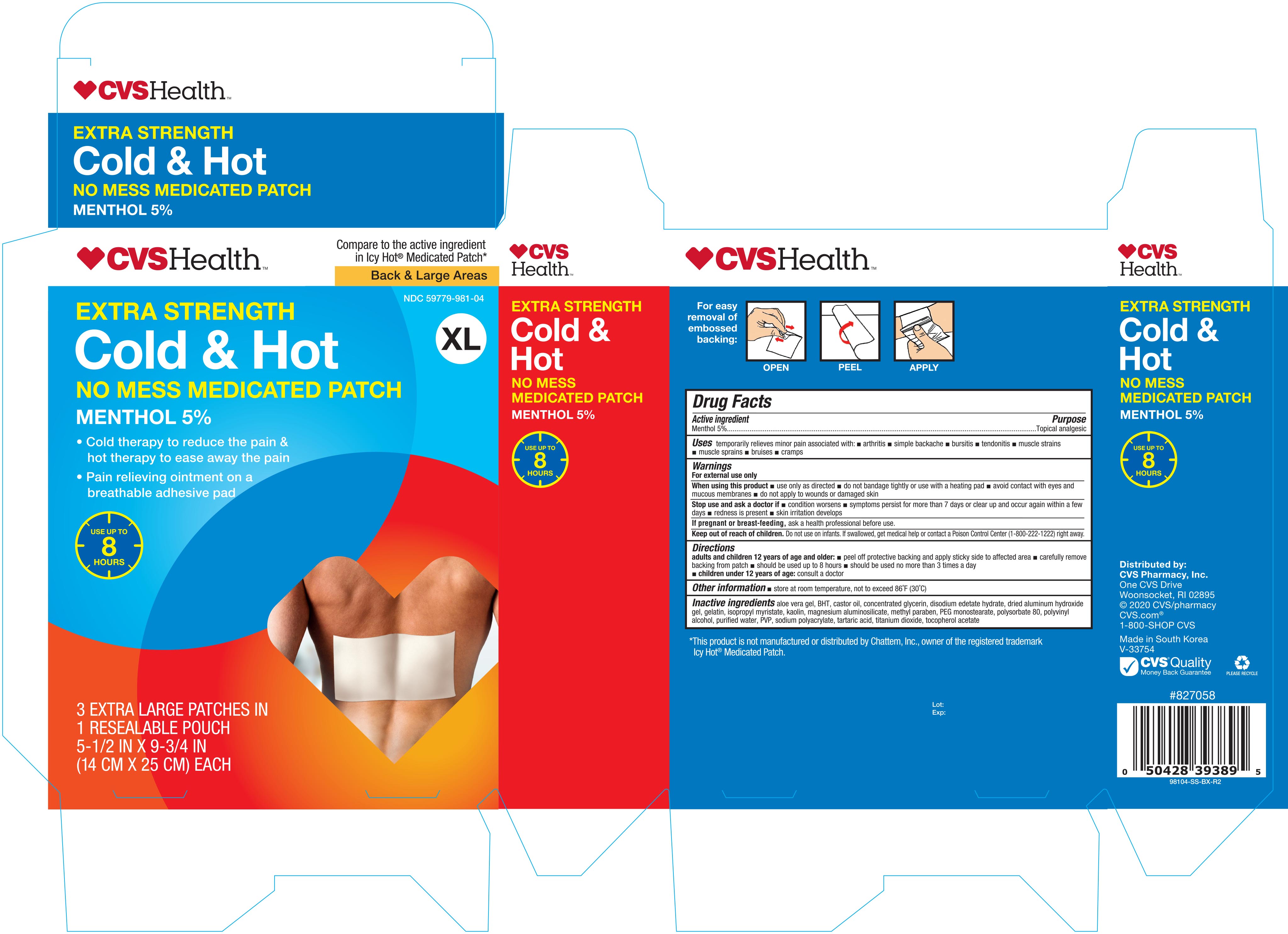 DRUG LABEL: CVS COLD AND HOT MEDICATED XL
NDC: 59779-981 | Form: PATCH
Manufacturer: CVS PHARMACY, INC.
Category: otc | Type: HUMAN OTC DRUG LABEL
Date: 20201002

ACTIVE INGREDIENTS: MENTHOL 750 mg/1 1
INACTIVE INGREDIENTS: GLYCERIN; POVIDONE, UNSPECIFIED; SODIUM POLYACRYLATE (8000 MW); .ALPHA.-TOCOPHEROL ACETATE; GELATIN; METHYLPARABEN; ALUMINUM HYDROXIDE; ISOPROPYL MYRISTATE; SILODRATE ANHYDROUS; EDETATE DISODIUM; ALOE VERA LEAF; BUTYLATED HYDROXYTOLUENE; CASTOR OIL; POLYSORBATE 80; POLYVINYL ALCOHOL, UNSPECIFIED; WATER; TARTARIC ACID; KAOLIN; TITANIUM DIOXIDE

CVS Cold & Hot Medicated XL Patch, 3ct (NBE Icyhot) SS, 98104, 2020

Active ingredient Purpose

Menthol 5% .....................................................................Topical analgesic

PURPOSE

Uses temporarily relieves minor pain associated with:

- arthritis
- simple backache
- bursitis
- tendonitis
- muscle strains
- muscle sprains
- bruises
- cramps

Warnings

For external use only

When using this product:

- use only as directed
- do not bandage tightly or use with heating pad
- avoid contact with eyes and mucous membranes
- do not apply to wounds or damaged skin

Stop use and ask a doctor if:

- condition worsens
- redness is present
- skin irritation develops
- symptoms persist for more than 7 days or clear up and occur again within a few days

PREGNANCY OR BREAST FEEDING

If pregnant or breast-feeding, ask a health professional before use.

Keep out of reach of children. Do not use on infants. If swallowed, get medical help or contact a Poison Control Center immediately

Directions

adults and children over 12 years:

- peel off protective backing and apply sticky side to affected area
- carefully remove backing from patch
- should be used up to 8 hours
- should be used no more than 3 times a day

children under 12 years:

consult a doctor

Other information

- store at room temperature, not to exceed 86°F (30°C)

Inactive ingredients

aloe vera gel, BHT, castor oil, concentrated glycerin, disodium edetate hydrate, dried aluminum hydroxide gel, gelatin, isopropyl myristate, kaolin, magnesium aluminosilicate, methyl paraben, PEG monostearate, polysorbate 80, polyvinyl alcohol, purified water, PVP, sodium polyacrylate, tartaric acid, titanium dioxide, tocopherol acetate

DOSAGE AND ADMINISTRATION

Distributed by:

CVS Pharmacy, Inc.

One CVS Drive, Woonsocket, RI 02895

www.cvs.com

Made in South Korea